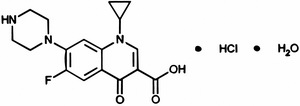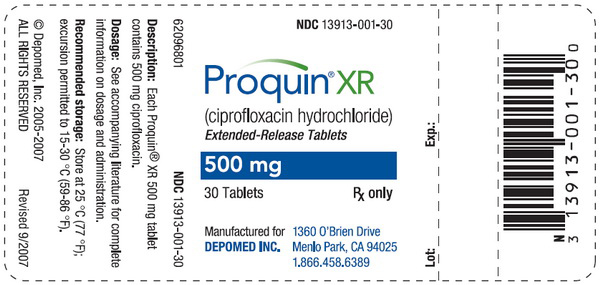 DRUG LABEL: Proquin
NDC: 13913-001 | Form: TABLET, FILM COATED, EXTENDED RELEASE
Manufacturer: Depomed, Inc.
Category: prescription | Type: HUMAN PRESCRIPTION DRUG LABEL
Date: 20100706

ACTIVE INGREDIENTS: CIPROFLOXACIN HYDROCHLORIDE 500 mg/1 1
INACTIVE INGREDIENTS: POVIDONE; MAGNESIUM STEARATE; POLYETHYLENE GLYCOL

Proquin® XR
(ciprofloxacin hydrochloride)
Extended-Release Tablets, 500 mg

BOXED WARNING

Fluoroquinolones, including Proquin XR, are associated with an increased risk of tendinitis and tendon rupture in all ages. The risk is further increased in older patients usually over 60 years of age, in patients taking corticosteroid drugs, and in patients with kidney, heart and lung transplant recipients (See WARNINGS).

To reduce the development of drug-resistant bacteria and maintain the effectiveness of Proquin XR and other antibacterial drugs, Proquin XR should be used only to treat uncomplicated urinary tract infections that are strongly suspected to be caused by bacteria.

DESCRIPTION

Proquin XR (ciprofloxacin hydrochloride) extended-release tablets contain ciprofloxacin hydrochloride, a synthetic broad-spectrum fluoroquinolone antimicrobial agent for oral administration.

Ciprofloxacin hydrochloride is 1-cyclopropyl-6-fluoro-1,4-dihydro-4-oxo-7-(1-piperazinyl)-3-quinolinecarboxylic acid hydrochloride. The molecular weight of the monohydrate is 385.82. It is a faintly yellowish to light yellow crystalline substance and its chemical structure is as follows:

Proquin XR is available as 500 mg (ciprofloxacin equivalent) tablets, utilizing AcuForm™ delivery technology. Proquin XR tablets are blue film-coated and oval-shaped. The inactive ingredients are povidone, magnesium stearate, polyethylene oxide, and film coating (Opadry® Blue).

CLINICAL PHARMACOLOGY

Absorption

When Proquin XR is administered with food, approximately 87% of ciprofloxacin is gradually released from the tablet over a 6-hour period. When administered following a meal maximum plasma ciprofloxacin concentrations are attained approximately 4.5-7 hours after dosing with Proquin XR tablets. Proquin XR should be administered with a main meal of the day, preferably the evening meal; if Proquin XR is given while fasting, the bioavailability will be lowered substantially. Administration of Proquin XR with a standardized meal (1000 calories, 50% fat) increased the Cmax and AUC0-24h by approximately 120% and 170%, respectively, compared to administration under fasting conditions; the mean Tmax was prolonged from 2.3 hours to 4.5 hours. The following table presents the pharmacokinetic parameters obtained at steady state for Proquin XR 500 mg qd versus CIPRO 250 mg bid.

Steady-State Pharmacokinetics for Ciprofloxacin in Plasma of Healthy Subjects (Day 3)a
Pharmacokinetic Parameters | Proquin XR 500 mg Tablets (qd) (n=27) | CIPRO 250 mg Tablets (bid) (n=27)
 | Mean (%CV)
AUC0-24h (mcg.hr/mL) | 7.67 (25) | 7.83 (16)
Cmax (mcg/mL) | 0.82 (28) | Cmax1 0.57 (25)b Cmax2 0.93 (27)
Cmin (mcg/mL) | 0.06 (42) | 0.14 (29)
 | Mean ± SD
Tmax (hr) | 6.1 ± 2.6 | Tmax1 2.5 ± 1.2c Tmax2 2.5 ± 1.4
a both treatments were administered following a standardized meal (approximately 1000 calories, 50% fat).
b Cmax1 = peak concentration after the evening dose of CIPRO bid.
Cmax2 = peak concentration after the morning dose of CIPRO bid.
c Tmax1 = time of peak concentration after the evening dose CIPRO bid.
Tmax2 = time of peak concentration after the morning dose CIPRO bid.

Distribution

The in vitro binding of ciprofloxacin to plasma proteins over a concentration ranging from 0.9 to 30 micromolar is 9.9% to 36.6%, which is not likely to cause clinically significant protein binding interactions with other drugs.

Metabolism

Four metabolites of ciprofloxacin have been identified in human urine and feces. The metabolites have antimicrobial activity, but are less active than unchanged ciprofloxacin. The metabolites are desethyleneciprofloxacin (M1), sulfociprofloxacin (M2), oxociprofloxacin (M3), and formylciprofloxacin (M4), which account for approximately 11% of the total dose.

Elimination

The plasma elimination half-life of ciprofloxacin in healthy volunteers following a Proquin XR 500 mg dose was approximately 4.5 hours. Following a 500 mg oral dose of Proquin XR, 26.9% was excreted in the urine over 24 hours as unchanged drug for both formulations.

Following administration of a single 500 mg dose of Proquin XR, approximately 41% of the oral dose was excreted into the urine over 96 hours as unchanged drug and metabolites. The urinary excretion of ciprofloxacin was virtually complete within 24 hours after dosing. Urinary excretion is a main route of elimination of ciprofloxacin and its urinary concentrations relative to the MICs of the bacterial species may be important to understanding the efficacy of ciprofloxacin for the treatment of urinary tract infections. The mean urinary ciprofloxacin concentration after dosing with Proquin XR 500 mg qd and CIPRO 250 mg bid are shown in the following table:

Mean Urinary Concentrations of Ciprofloxacin
Treatment | Day | Mean (%CV) urinary ciprofloxacin concentration over 24 hours (mcg/mL)
Proquin XR 500 mg once daily | 1 | 71 (41)
Proquin XR 500 mg once daily | 3 | 67 (28)
CIPRO 250 mg twice daily | 1 | 79 (32)
CIPRO 250 mg twice daily | 3 | 75 (24)

The renal clearance of ciprofloxacin following administration of Proquin XR, which is approximately 304-383 mL/minute, exceeds the normal glomerular filtration rate of 120 mL/minute. Thus, active tubular secretion would seem to play a significant role in its elimination.

Approximately 43% of the oral dose of Proquin XR is recovered from the feces as unchanged drug and metabolites within 7 days after dosing. This may arise from either biliary clearance or transintestinal elimination.

Drug Interactions

Antacids: The interaction of Proquin XR (administered as a single 1000 mg [2 x 500 mg] dose) and magnesium/aluminum-containing antacids (900 mg aluminum hydroxide and 600 mg magnesium hydroxide administered as a single oral dose) was evaluated in healthy volunteers. When Proquin XR was given 2 hours after antacids and 6 hours before antacids, the Cmax values were similar to those when Proquin XR was given alone and AUC values were reduced by approximately 10%. When Proquin XR was given 4 hours before antacids, Cmax was reduced by approximately 11% and AUC was reduced by approximately 22%. Thus, to minimize the effect of antacids on the absorption of ciprofloxacin, Proquin XR should be given either 2 hours after or at least 4 hours before antacids (see PRECAUTIONS: Drug Interactions, and Information for Patients).

Caffeine: Some quinolones, including ciprofloxacin also decrease caffeine clearance and inhibit the formation of paraxanthine after caffeine administration. (See PRECAUTIONS: Drug Interactions)

Calcium-containing beverages: Concomitant administration of ciprofloxacin with milk products or calcium-fortified juices alone should be avoided since decreased absorption is possible. (See PRECAUTIONS: Drug Interactions and Information for Patients, and DOSAGE AND ADMINISTRATION)

Histamine H2-receptor antagonists: Histamine H2-receptor antagonists appear to have no significant effect on the bioavailability of ciprofloxacin.

Metronidazole: The serum concentrations of ciprofloxacin and metronidazole were not altered when these two drugs were given concomitantly.

Multivalent cation-containing products: Concomitant administration of ciprofloxacin with sucralfate, VIDEX® (didanosine) chewable/buffered tablets, metal cations such as iron and calcium, and multivitamin preparations with zinc should be avoided. (See PRECAUTIONS: Drug Interactions and Information for Patients)

Omeprazole: When Proquin XR was administered following a meal as a single 1000 mg dose (2 x 500 mg), 2 hours after the third dose of omeprazole (given 40 mg once daily for three days) to 27 healthy volunteers, the mean AUC and Cmax of ciprofloxacin were bioequivalent to the mean AUC and Cmax values when Proquin XR was administered alone. Omeprazole should be taken as directed and Proquin XR should be taken with a main meal of the day, preferably the evening meal. (See PRECAUTIONS: Drug Interactions and Information for Patients)

Probenecid: Co-administration of probenecid with fluoroquinolones results in a reduction in the renal clearance and an increase in their concentrations in the systemic circulation.

Theophylline: Previous studies with quinolones, including ciprofloxacin, have shown that concomitant administration of these drugs with theophylline decreases the clearance of theophylline resulting in elevated serum theophylline levels and increased risk of a patient developing central nervous system (CNS) or other adverse reactions. (See WARNINGS, PRECAUTIONS: Drug Interactions)

Warfarin: Ciprofloxacin and other quinolones have been reported to enhance the effects of the oral anticoagulant, warfarin, or its derivatives. When these products are administered concomitantly, prothrombin time or other suitable coagulation tests should be closely monitored. The co-administration of single doses of Proquin XR and Coumadin® (7.5 mg) did not result in significant changes in the pharmacokinetics of ciprofloxacin nor did it significantly affect the pharmacodynamics of S-warfarin and R-warfarin. Although the Cmax and AUC of the two warfarin enantiomers and the elimination half-life of S-warfarin were not significantly altered by ciprofloxacin co-administration, the half-life of R-warfarin was statistically significantly prolonged (P=0.029). (See PRECAUTIONS: Drug Interactions)

Special Populations

Elderly: When a single 500 mg dose of Proquin XR was administered to elderly subjects (>65 years) Cmax and AUC values were increased by approximately 24% and 20% respectively, compared to younger subjects from a reference study. This can be at least partially attributed to decreased renal clearance in the elderly. However, in elderly subjects, the percentage of the ciprofloxacin dose excreted in the urine was 11% lower as compared to younger subjects. The elimination half-life was not significantly prolonged in elderly subjects (4.9 hours) compared to healthy young subjects (4.5 hours). These differences are not considered clinically significant. (See PRECAUTIONS: Geriatric Use)

Renal Impairment: After receiving a single dose of Proquin XR 500 mg, the ciprofloxacin AUC0-24h in subjects with mild renal impairment (CLcr = 51-80 mL/min; n=10) and moderate renal impairment (CLcr = 30-50 mL/min; n=10) were 42% and 54% greater, respectively, compared to subjects with normal renal function (CLcr >80 mL/min; n=10). The elimination half-life of ciprofloxacin in patients with mild and moderate renal impairment was approximately 1.7 times longer as compared to the control group (7.8-7.5 hours versus 4.5 hours). In patients with end-stage renal disease (CLcr <10 mL/min), the half-life of ciprofloxacin is approximately doubled compared to subjects with normal renal function. No dose adjustment of Proquin XR is required for patients with uUTI and mild to moderate renal impairment. The efficacy of Proquin XR has not been studied in patients with severe renal impairment. (See DOSAGE AND ADMINISTRATION)

Altered Liver Function: In studies in patients with stable chronic cirrhosis, no significant changes in ciprofloxacin pharmacokinetics have been observed. The pharmacokinetics of ciprofloxacin in patients with acute hepatic insufficiency, however, has not been fully elucidated. (See DOSAGE AND ADMINISTRATION)

Pediatrics: The pharmacokinetics of Proquin XR have not been studied in pediatric populations.

MICROBIOLOGY

Ciprofloxacin has in vitro activity against a wide range of gram-negative and gram-positive organisms. The bactericidal action of ciprofloxacin results from inhibition of topoisomerase II (DNA gyrase) and topoisomerase IV (both Type II topoisomerases) which are required for bacterial DNA replication, transcription, repair and recombination. The mechanism of action of quinolones, including ciprofloxacin, is different from that of other antimicrobial agents such as beta-lactams, macrolides, tetracyclines, or aminoglycosides; therefore, organisms resistant to these drugs may be susceptible to ciprofloxacin. There is no known cross-resistance between ciprofloxacin and other classes of antimicrobials. Resistance to ciprofloxacin in vitro develops slowly (multiple step mutation). Resistance to ciprofloxacin due to spontaneous mutations occurs at a general frequency of between <10^-9 to 1x10^-6.

Ciprofloxacin is less active when tested at acidic pH. The inoculum size has little effect when tested in vitro. The minimal bactericidal concentration (MBC) generally does not exceed the MIC by more than a factor of 2.

Ciprofloxacin has been shown to be active against most strains of the following organisms, both in vitro and in clinical infections as described in the INDICATIONS AND USAGE section.

Aerobic gram-negative microorganisms
Escherichia coli
Klebsiella pneumoniae

The following in vitro data are available, but their clinical significance is unknown.

Ciprofloxacin exhibits in vitro MICs of 1 mcg/mL or less against most (>90%) strains of the following microorganisms; however, the safety and effectiveness of Proquin XR in treating clinical infections due to these microorganisms have not been established in adequate and well-controlled clinical trials.

Aerobic gram-negative microorganisms
Proteus mirabilis

Susceptibility Tests

Interpretive criteria for urinary isolates have not been established for Proquin XR. Interpretive criteria established based on systemic drug levels may not be appropriate for uncomplicated urinary tract infections.

Dilution Techniques: Quantitative methods are used to determine antimicrobial minimum inhibitory concentrations (MICs). These MICs provide estimates of the susceptibility of bacteria to antimicrobial compounds. The MICs should be determined using a standardized procedure. Standardized procedures are based on a dilution method^1 (broth or agar) or equivalent with standardized inoculum concentrations and standardized concentrations of ciprofloxacin powder. The MIC values should be interpreted according to the following criteria:

For testing Enterobacteriaceae:

MIC (mcg/mL) | Interpretation
≤ 1 | Susceptible (S)
2 | Intermediate (I)
≥ 4 | Resistant (R)

A report of "Susceptible" indicates that the pathogen is likely to be inhibited if the antimicrobial compound in the blood reaches the concentration usually achievable. A report of "Intermediate" indicates that the result should be considered equivocal, and if the microorganism is not fully-susceptible to alternative, clinically feasible drugs, the test should be repeated. This category implies possible clinical applicability in body sites where the drug is physiologically concentrated or in situations where high dosage of drug can be used. This category also provides a buffer zone which prevents small uncontrolled technical factors from causing major discrepancies in interpretation. A report of "Resistant" indicates that the pathogen is not likely to be inhibited if the antimicrobial compound in the blood reaches the concentration usually achievable; other therapy should be selected.

Standardized susceptibility test procedures require the use of laboratory control microorganisms to control the technical aspects of the laboratory procedures. Standard ciprofloxacin powder should provide the following MIC values:

Microorganism |  | MIC Range (mcg/mL)
Escherichia coli | ATCC 25922 | 0.004-0.015
Staphylococcus aureus | ATCC 29213 | 0.12-0.5

Diffusion Techniques: Quantitative methods that require measurement of zone diameters also provide reproducible estimates of the susceptibility of bacteria to antimicrobial compounds. One such standardized procedure^2 requires the use of standardized inoculum concentrations. This procedure uses paper disks impregnated with 5-mcg ciprofloxacin to test the susceptibility of microorganisms to ciprofloxacin.

Reports from the laboratory providing results of the standard single-disk susceptibility test with a 5-mcg ciprofloxacin disk should be interpreted according to the following criteria:

For testing Enterobacteriaceae:

Zone Diameter (mm) | Interpretation
≥ 21 | Susceptible (S)
16-20 | Intermediate (I)
≤ 15 | Resistant (R)

Interpretation should be as stated above for results using dilution techniques. Interpretation involves correlation of the diameter obtained in the disk test with the MIC for ciprofloxacin.

As with standardized dilution techniques, diffusion methods require the use of laboratory control microorganisms that are used to control the technical aspects of the laboratory procedures. For the diffusion technique, the 5-mcg ciprofloxacin disk should provide the following zone diameters in these laboratory quality control strains:

Microorganism |  | Zone Diameter (mm)
Escherichia coli | ATCC 25922 | 30-40
Staphylococcus aureus | ATCC 25923 | 22-30

INDICATIONS AND USAGE

Proquin XR is indicated only for the treatment of uncomplicated urinary tract infections (acute cystitis) caused by susceptible strains of the designated microorganisms listed below. Proquin XR is not interchangeable with other ciprofloxacin extended-release or immediate release oral formulations. See DOSAGE AND ADMINISTRATION for specific recommendations.

Uncomplicated urinary tract infections (acute cystitis) caused by Escherichia coli and Klebsiella pneumoniae.

THE SAFETY AND EFFICACY OF PROQUIN XR IN TREATING PYELONEPHRITIS, COMPLICATED URINARY TRACT INFECTIONS, AND INFECTIONS OTHER THAN UNCOMPLICATED URINARY TRACT INFECTIONS HAVE NOT BEEN DEMONSTRATED. Alternative therapy should be considered for patients who remain symptomatic or develop fever and back pain while on treatment with Proquin XR.

To reduce the development of drug-resistant bacteria and maintain the effectiveness of Proquin XR and other antibacterial drugs, Proquin XR should only be used to treat uncomplicated urinary tract infections that are proven or strongly suspected to be caused by susceptible bacteria. When culture and sensitivity information are available, they should be considered in selecting or modifying antibacterial therapy. In the absence of such data, local epidemiology and susceptibility patterns may contribute to the empiric selection of therapy.

CONTRAINDICATIONS

Proquin XR is contraindicated in persons with a history of hypersensitivity to ciprofloxacin or any member of the quinolone class of antimicrobial agents, or any of the product components.

WARNINGS

Tendinopathy and Tendon Rupture: Fluoroquinolones, including Proquin XR, are associated with an increased risk of tendinitis and tendon rupture in all ages. This adverse reaction most frequently involves the Achilles tendon, and rupture of the Achilles tendon may require surgical repair. Tendinitis and tendon rupture in the rotator cuff (the shoulder), the hand, the biceps, the thumb, and other tendon sites have also been reported. The risk of developing fluoroquinolone-associated tendinitis and tendon rupture is further increased in older patients usually over 60 years of age, in patients taking corticosteroid drugs, and in patients with kidney, heart or lung transplants. Factors, in addition to age and corticosteroid use, that may independently increase the risk of tendon rupture include strenuous physical activity, renal failure, and previous tendon disorders such as rheumatoid arthritis. Tendinitis and tendon rupture have also occurred in patients taking fluoroquinolones who do not have the above risk factors. Tendon rupture can occur during or after completion of therapy; cases occurring up to several months after completion of therapy have been reported. Proquin XR should be discontinued if the patient experiences pain, swelling, inflammation or rupture of a tendon. Patients should be advised to rest at the first sign of tendinitis or tendon rupture, and to contact their healthcare provider regarding changing to a non- quinolone antimicrobial drug.

THE SAFETY AND EFFECTIVENESS OF PROQUIN XR IN PEDIATRIC PATIENTS AND ADOLESCENTS (LESS THAN 18 YEARS OF AGE), PREGNANT WOMEN, AND LACTATING WOMEN HAVE NOT BEEN ESTABLISHED. (See PRECAUTIONS: Pediatric Use, Pregnancy, and Nursing Mothers subsections)

Ciprofloxacin, as with other members of the quinolone class, causes arthropathy and/or chondroplasia in immature dogs. Related quinolone-class drugs also produce erosions of cartilage of weight-bearing joints and other signs of arthropathy in immature animals of various species. The relevance of these findings to the clinical use of ciprofloxacin is unknown. (See ANIMAL PHARMACOLOGY)

Central Nervous System: Convulsions, increased intracranial pressure, and toxic psychosis have been reported in patients receiving quinolones, including ciprofloxacin. Ciprofloxacin may also cause CNS events including: dizziness, confusion, tremors, hallucinations, depression, and, rarely, suicidal thoughts or acts. The reactions may occur following the first dose. If these reactions occur in patients receiving ciprofloxacin, the drug should be discontinued and appropriate measures instituted. As with all quinolones, ciprofloxacin should be used with caution in patients with known or suspected CNS disorders that may predispose to seizures or lower the seizure threshold (e.g., severe cerebral arteriosclerosis, epilepsy), or in the presence of other risk factors that may predispose to seizures or lower the seizure threshold (e.g., certain drug therapy, renal dysfunction). (See PRECAUTIONS: General, Information for Patients, Drug Interactions, and ADVERSE REACTIONS)

Theophylline: SERIOUS AND FATAL REACTIONS HAVE BEEN REPORTED IN PATIENTS RECEIVING CONCURRENT ADMINISTRATION OF FLUOROQUINOLONES, INCLUDING CIPROFLOXACIN, AND THEOPHYLLINE. These reactions have included cardiac arrest, seizure, status epilepticus, and respiratory failure. Although similar adverse effects have been reported in patients receiving theophylline alone, the possibility that these reactions may be potentiated by Proquin XR cannot be eliminated. If concomitant use cannot be avoided, serum levels of theophylline should be monitored and dosage adjustments made as appropriate.

Hypersensitivity Reactions: Other serious and sometimes fatal events, some due to hypersensitivity, and some due to uncertain etiology, have been reported rarely in patients receiving therapy with quinolones, including ciprofloxacin. These events may be severe and generally occur following the administration of multiple doses. Clinical manifestations may include one or more of the following:

- fever, rash or severe dermatologic reactions (e.g., toxic epidermal necrolysis, Stevens-Johnson Syndrome);
- vasculitis; arthralgia; myalgia; serum sickness;
- allergic pneumonitis
- inertstitial nephritis; acute renal insufficiency or failure;
- hepatitis; jaundice; acute hepatic necrosis or failure;
- anemia, including hemolytic and apalstic; thrombocytopenia, including thrombotic thrombocytopenic purpura; leukopenia; agranulocytosis; pancytopenia; and/or other hemtologic abnormalities.

The drug should be discontinued immediately at the first appearance of a skin rash, jaundice, or any other sign of hypersensitivity and supportive measures instituted (See PRECAUTIONS: Information for Patients and ADVERSE REACTIONS).

Clostridium difficile associated diarrhea (CDAD) has been reported with use of nearly all antibacterial agents, including Proquin XR, and may range in severity from mild diarrhea to fatal colitis. Treatment with antibacterial agents alters the normal flora of the colon leading to overgrowth of C. difficile.

C. difficile produces toxins A and B which contribute to the development of CDAD. Hypertoxin producing strains of C. difficile cause increased morbidity and mortality, as these infections can be refractory to antimicrobial therapy and may require colectomy. CDAD must be considered in all patients who represent with diarrhea following antibiotic use. Careful medical history is necessary since CDAD has been reported to occur over two months after the administration of antibacterial agents.

If CDAD is suspected or confirmed, ongoing antibiotic use not directed against C. difficile may need to be discontinued. Appropriate fluid and electrolyte management, protein supplementation, antibiotic treatment of C. difficile, and surgical evaluation should be instituted as clinically indicated.

Peripheral Neuropathy: Rare cases of sensory or sensorimotor axonal polyneuropathy affecting small and/or large axons resulting in paresthesias, hypoesthesias, dyesthesias, and weakness have been reported in patients receiving quinolones, including ciprofloxacin. Ciprofloxacin should be discontinued if the patient experiences symptoms of neuropathy, including pain, burning, tingling, numbness, and/or weakness, or is found to have deficits in light touch, pain, temperature, position, sense, vibratory sensation, and/or motor strength in order to prevent the development of an irreversible condition.

PRECAUTIONS

General

Crystals of ciprofloxacin have been observed rarely in the urine of human subjects but more frequently in the urine of laboratory animals, which is usually alkaline. (See ANIMAL PHARMACOLOGY). Crystalluria related to ciprofloxacin has been reported only rarely in humans because human urine is usually acidic. Alkalinity of the urine should be avoided in patients receiving ciprofloxacin. Patients should be well hydrated to prevent the formation of highly concentrated urine.

Quinolones, including ciprofloxacin, may also cause CNS events, including nervousness, agitation, insomnia, anxiety, nightmares, or paranoia. (See WARNINGS)

Moderate to severe photosensitivity/ phototoxicity reactions, the latter of which may manifest as exaggerated sunburn reactions (e.g., burning, erythema, exudation, vesicles, blistering, edema) involving areas exposed to light (typically the face, "V" area of the neck, extensor surfaces of the forearms, dorsa of the hands), can be associated with the use of quinolone antibiotics after sun or UV light exposure. Therefore, excessive exposure to these sources of light should be avoided. Drug therapy should be discontinued if phototoxicity occurs (See ADVERSE REACTIONS and ADVERSE REACTIONS/ Post-Marketing Adverse Events).

Prescribing Proquin XR in the absence of a strongly suspected bacterial infection is unlikely to benefit the patient and increases the risk of the development of drug-resistant bacteria.

Information for Patients

Patients should be advised:

- to contact their healthcare provider if they experience pain, swelling, or inflammation of a tendon, or weakness or inability to use one of their joints; rest and refrain from exercise; and discontinue Proquin XR treatment. The risk of severe tendon disorders with fluoroquinolones is higher in older patients usually over 60 years of age, in patients taking corticosteroid drugs, and in patients with kidney, heart or lung transplants.
- that antibacterial drugs, including Proquin XR, should only be used to treat bacterial infections. They do not treat viral infections (e.g., the common cold). When Proquin XR is prescribed to treat a bacterial infection, patients should be told that although it is common to feel better early in the course of therapy, the medication should be taken exactly as directed. Skipping doses or not completing the full course of therapy may (1) decrease the effectiveness of the immediate treatment and (2) increase the likelihood that bacteria will develop resistance and will not be treatable by Proquin XR or other antibacterial drugs in the future.
- that Proquin XR should only be used to treat uncomplicated urinary tract infections (also known as bladder infections). The safety and efficacy of Proquin XR to treat other urinary tract or non-urinary tract infections have not been studied.
- that Proquin XR should be taken with a main meal of the day, preferably the evening meal. The patient should not take more than one Proquin XR tablet per day, even if the patient misses a dose.
- that Proquin XR tablets should be taken whole and never split, crushed, or chewed.
- that concomitant administration of Proquin XR with aluminum or magnesium-containing antacids, sucralfate, VIDEX® (didanosine) chewable buffered tablets or pediatric powder, metal cations such as iron and calcium, and multivitamin preparations containing zinc should be avoided. Proquin XR should be administered at least 4 hours before or 2 hours after these products. (See CLINICAL PHARMACOLOGY: Drug Interactions, DOSAGE AND ADMINISTRATION, and PRECAUTIONS: Drug Interactions)
- that Proquin XR should not be taken with dairy products (like milk or yogurt) or calcium-fortified juices alone, since the absorption of ciprofloxacin may be significantly reduced. However, Proquin XR may be taken with a meal that contains these products. (See CLINICAL PHARMACOLOGY: Drug Interactions and PRECAUTIONS: Drug Interactions)
- that ciprofloxacin may be associated with hypersensitivity reactions, even following a single dose, and to discontinue Proquin XR at the first sign of a skin rash or other allergic reaction and contact their physician.
- that photosensitivity/ phototoxicity has been reported in patients receiving quinolone antibiotics. Patients should minimize or avoid exposure to natural or artificial sunlight (tanning beds or UVA/B treatment) while taking quinolones. If patients need to be outdoors while using quinolones, they should wear loose-fitting clothes that protect the skin from sun exposure and discuss other sun protection measures with their physician. If a sunburn-like reaction or skin eruption occurs, patients should contact their physician;
- that peripheral neuropathies have been associated with ciprofloxacin use. If symptoms of peripheral neuropathy including pain, burning, tingling, numbness and/or weakness develop, patients should discontinue treatment and contact their physician.
- to contact their doctor if they do not feel better or if they develop fever and back pain while or after taking Proquin XR.
- that Proquin XR may cause dizziness and lightheadedness; therefore, patients should know how they react to this drug before they operate an automobile or machinery or engage in activities requiring mental alertness or coordination.
- that Proquin XR may increase the effects of theophylline and caffeine. There is a possibility of caffeine accumulation when products containing caffeine are consumed while taking quinolones.
- that convulsions have been reported in patients receiving quinolones, including ciprofloxacin, and to notify their physician before taking this drug if there is a history of this condition.
- that diarrhea is a common problem caused by antibiotics which usually ends when the antibiotic is discontinued. Sometimes after starting treatment with antibiotics, patients can develop watery and bloody stools (with or without stomach cramps and fever) even as late as two or more months after having taken the last dose of the antibiotic. If this occurs, patients should contact their physician as soon as possible.

Drug Interactions

Caffeine: Some quinolones, including ciprofloxacin, have also been shown to interfere with the metabolism of caffeine. This may lead to reduced clearance of caffeine and a prolongation of its serum half-life.

Cyclosporine: Some quinolones, including ciprofloxacin, have been associated with transient elevations in serum creatinine in patients receiving cyclosporine concomitantly.

Glyburide: The concomitant administration of ciprofloxacin with the sulfonylurea glyburide has, on rare occasions, resulted in severe hypoglycemia.

Histamine H2-receptor antagonists: Histamine H2-receptor antagonists appear to have no significant effect on the bioavailability of ciprofloxacin.

Methotrexate: Renal tubular transport of methotrexate may be inhibited by concomitant administration of ciprofloxacin, potentially leading to increased plasma levels of methotrexate. This might increase the risk of methotrexate toxic reactions. Therefore, patients under methotrexate therapy should be carefully monitored when concomitant ciprofloxacin therapy is indicated.

Multivalent cation-containing products: Concurrent administration of a quinolone, including ciprofloxacin, with multivalent cation-containing products such as magnesium or aluminum antacids, sucralfate, VIDEX® chewable/buffered tablets or pediatric powder, or products containing calcium, iron, or zinc may substantially decrease the absorption of ciprofloxacin, resulting in serum and urine levels considerably lower than desired. Proquin XR should be administered at least 4 hours before or 2 hours after these products. This time window is different than for other oral formulations of ciprofloxacin, which are usually administered 2 hours before or 6 hours after antacids. (See CLINICAL PHARMACOLOGY: Drug Interactions, PRECAUTIONS: Information for Patients, and DOSAGE AND ADMINISTRATION)

Non-steroidal anti-inflammatory drugs (but not aspirin): These drugs in combination with very high doses of quinolones have been shown to provoke convulsions in pre-clinical studies.

Omeprazole: The rate and extent of absorption of ciprofloxacin was bioequivalent when Proquin XR was given alone or when Proquin XR was given 2 hours after omeprazole at the dose that maximally suppresses gastric acid secretion. Omeprazole should be taken as directed and Proquin XR should be taken with a main meal of the day, preferably the evening meal. (See CLINICAL PHARMACOLOGY: Drug Interactions and Information for Patients).

Phenytoin: Altered serum levels of phenytoin (increased and decreased) have been reported in patients receiving concomitant ciprofloxacin.

Probenecid: Probenecid interferes with renal tubular secretion of ciprofloxacin and produces an increase in the level of ciprofloxacin in serum.

Theophylline: As with some other quinolones, concurrent administration of ciprofloxacin with theophylline may lead to elevated serum concentrations of theophylline and prolongation of its elimination half-life. This may result in increased risk of theophylline-related adverse reactions. (See WARNINGS) If concomitant use cannot be avoided, serum levels of theophylline should be monitored and dosage adjustments made as appropriate.

Warfarin: Quinolones have been reported to enhance the effects of the oral anticoagulant warfarin or its derivatives. When these products are administered concomitantly, prothrombin time or other suitable coagulation tests should be monitored.

Carcinogenesis, Mutagenesis, Impairment of Fertility

Rodent carcinogenicity studies were not required. Two in vitro mutagenicity tests were conducted with ciprofloxacin:

- Bacterial Reverse Mutation Assay; negative for mutagenicity in the presence and absence of an S-9 metabolic activation system.
- Chinese Hamster Ovary (CHO) Chromosomal Aberration Assay; positive for inducing chromosomal aberrations.

In addition to the in vitro genotoxicity assays, an in vivo rat micronucleus study with ciprofloxacin was negative.

Fertility studies performed with male and female rats at oral doses of ciprofloxacin up to 600 mg/kg/day (approximately 10-fold the recommended 500 mg therapeutic dose based upon body surface area) revealed no evidence of impairment.

Pregnancy: Teratogenic Effects. Pregnancy Category C

There are no adequate and well-controlled studies of Proquin XR in pregnant women. An expert review of published data on experiences with ciprofloxacin use during pregnancy by TERIS - the Teratogen Information System - concluded that therapeutic doses during pregnancy are unlikely to pose a substantial teratogenic risk (quantity and quality of data = fair), but the data are insufficient to state that there is no risk.

A controlled prospective observational study followed 200 women exposed to fluoroquinolones (52.5% exposed to ciprofloxacin and 68% first trimester exposures) during gestation. In utero exposure to fluoroquinolones during embryogenesis was not associated with increased risk of major malformations. The reported rates of major congenital malformations were 2.2% for the fluoroquinolone group and 2.6% for the control group (background incidence of major malformations is 1-5%). Rates of spontaneous abortions, prematurity and low birth weight did not differ between the groups and there were no clinically significant musculoskeletal dysfunctions up to one year of age in the ciprofloxacin exposed children.

Another prospective follow up study reported on 549 pregnancies with fluoroquinolone exposure (93% first trimester exposures). There were 70 ciprofloxacin exposures, all within the first trimester. The malformation rates among live-born babies exposed to ciprofloxacin and to fluoroquinolones overall were both within background incidence ranges. No specific patterns of congenital abnormalities were found. The study did not reveal any clear adverse reactions due to in utero exposure to ciprofloxacin.

No differences in the rates of prematurity, spontaneous abortions, or birth weight were seen in women exposed to ciprofloxacin during pregnancy. However, these small postmarketing epidemiology studies, of which most experience is from short term first semester exposure, are insufficient to evaluate the risk for less common defects or to permit reliable and definitive conclusions regarding the safety of ciprofloxacin in pregnant women and their developing fetuses. Ciprofloxacin should not be used during pregnancy unless the potential benefit justifies the potential risk to both fetus and mother (see WARNINGS).

Embryo/fetal developmental toxicity studies were conducted in pregnant rats and rabbits using oral doses up to 600 mg/kg/day in rats and 30 mg/kg/day in rabbits. Fetal development (skeletal variation) was affected in rats at the maternally toxic dose of 600 mg/kg/day (approximately 1.8-fold the recommended 500 mg therapeutic dose based upon plasma AUC measure of systemic exposure). The maternally toxic 30 mg/kg/day dose to pregnant rabbits resulted in abortions and body weight gain depression; embryo/fetal lethality and skeletal developmental effects were observed at this dose level (approximately 1.2-fold the recommended therapeutic dose based upon body surface area). The 10 mg/kg/day dose level, although maternally toxic, did not induce embryo/fetal developmental effects. A peri/postnatal developmental toxicity study with pregnant/lactating female rats exhibited no developmental effects to the F1 pups at the highest dose level of 600 mg/kg/day; the 300 and 600 mg/kg/day dose levels were maternally toxic to the pregnant dams based upon slight body weight gain reduction. No evidence of compound-related fetal malformation was observed in any of the reproductive toxicity studies.

Nursing Mothers

Ciprofloxacin is excreted in human milk. The amount of ciprofloxacin absorbed by the nursing infant is unknown. Because of the potential for serious adverse reactions in infants nursing from mothers taking ciprofloxacin, a decision should be made whether to discontinue nursing or to discontinue ciprofloxacin taking into account the importance of the drug to the mother.

Pediatric Use

The safety and effectiveness of Proquin XR in pediatric patients and adolescents less than 18 years of age have not been established. Quinolones, including ciprofloxacin, cause arthropathy in juvenile animals. (See WARNINGS)

Geriatric Use

Geriatric patients are at increased risk for developing severe tendon disorders including tendon rupture when being treated with a fluoroquinolone such as Proquin XR. This risk is further increased in patients receiving concomitant corticosteroid therapy. Tendinitis or tendon rupture can involve the Achilles, hand, shoulder, or other tendon sites and can occur during or after completion of therapy; cases occurring up to several months after fluoroquinolone treatment have been reported. Caution should be used when prescribing Proquin XR to elderly patients especially those on corticosteroids. Patients should be informed of this potential side effect and advised to discontinue Proquin XR and contact their healthcare provider if any symptoms of tendinitis or tendon rupture occur (See Boxed Warning, WARNINGS, and ADVERSE REACTIONS/ Post-Marketing Adverse Event Reports).

Clinical experience with Proquin XR did not include sufficient number of subjects 65 years of age or older to determine whether they respond differently than younger subjects. Reported clinical experience with other formulations of ciprofloxacin has not identified differences in responses between elderly and younger patients, but greater sensitivity of some older individuals on any drug therapy cannot be ruled out. Ciprofloxacin is substantially excreted by the kidney and the risk of adverse reactions may be greater in patients with impaired renal function. No alteration of dosage is necessary for patients greater than 65 years of age with normal renal function. (See CLINICAL PHARMACOLOGY and DOSAGE AND ADMINISTRATION)

In general, elderly patients may be more susceptible to drug-associated effects on the QT interval. Therefore, precaution should be taken when using Proquin XR with concomitant drugs that can result in prolongation of the QT interval (e.g. class IA or class III antiarrhythmics) or in patients with risk factors for torsades de pointes (e.g., known QT prolongation, uncorrected hypokalemia).

ADVERSE REACTIONS

Two clinical trials enrolled 1,095 patients, of whom 547 patients received Proquin XR 500 mg once daily and 538 patients received CIPRO 250 mg twice daily for 3 days. The patients were followed for approximately 5 weeks after the end of study drug dosing. Most adverse events reported were described as mild to moderate in severity and required no treatment. Proquin XR was discontinued due to adverse reactions thought to be drug-related in 0.5% of patients.

The incidence of all adverse events (regardless of relationship to study drug) reported for at least 2% of patients treated with Proquin XR during the entire 5-week study period was as follows: fungal infection (2.6%), nasopharyngitis (2.6%), headache (2.4%), and micturition urgency (2.0%).

The incidence of adverse events (regardless of relationship to study drug) reported for at least 1% of patients treated with Proquin XR during study drug treatment and up to 3 days after study drug was headache (1.5%).

The incidence of adverse events, judged by investigators to be at least possibly drug-related, occurring any time during the study in at least 1% of Proquin XR-treated patients was fungal infection (1.6%).

Additional uncommon events, judged by the investigator to be at least possibly drug-related, occurring at any time during the study in less than 1% of Proquin XR-treated patients were:

Cardiac Disorders: ventricular bigeminy.

Immune System Disorders: hypersensitivity.

Gastrointestinal Disorders: abdominal pain, nausea, diarrhea, dyspepsia, aggravated irritable bowel syndrome, lower abdominal pain, vomiting.

General Disorders: suprapubic pain, fatigue, pain, rigors, tenderness.

Infections and Infestations: urinary tract infection, fungal vaginosis, bacterial vaginitis, vaginal candidiasis, vaginal infection, vaginitis.

Investigations: blood bilirubin increased, alanine aminotransferase increased, abdominal aortic bruit, aspartate aminotransferase increased, body temperature increased.

Musculoskeletal and Connective Tissue Disorders: joint swelling, muscle spasms, night cramps.

Nervous System Disorders: headache, dizziness, disturbance in attention, paresthesia.

Renal and Urinary Disorders: micturition urgency, dysuria, urinary frequency, abnormal urine odor.

Reproductive System and Breast Disorders: female genital pruritus.

Respiratory, Thoracic, and Mediastinal Disorders: dyspnea.

Skin/Subcutaneous Tissue Disorders: rash, photosensitivity/ phototoxicity reaction, pruritus, urticaria.

Reported Post-Marketing Adverse Events with Other Formulations of Ciprofloxacin

The following adverse events, some of them life threatening, regardless of incidence or relationship to drug, have been reported during clinical trials and from worldwide post-marketing experience in patients given ciprofloxacin (includes all formulations, all dosages, all drug-therapy, and all indications). Because these reactions have been reported voluntarily from a population of uncertain size, it is not always possible to reliably estimate their frequency or a causal relationship to drug exposure. The events in alphabetical order are:

Abnormal gait, achiness, acidosis, agitation, agranulocytosis, allergic reactions (ranging from urticaria to anaphylactic reactions), amylase increase, anemia, angina pectoris, angioedema, anosmia, anxiety, arrhythmia, arthralgia, ataxia, atrial flutter, bleeding diathesis, blurred vision, bronchospasm, C. difficile associated diarrhea, candidiasis (cutaneous, oral), candiduria, cardiac murmur, cardiopulmonary arrest, cardiovascular collapse, cerebral thrombosis, chills, cholestatic jaundice, chromatopsia, confusion, convulsion, delirium, depression, diplopia, drowsiness, dysphagia, dyspnea, edema (conjunctivae, face, hands, laryngeal, lips, lower extremities, neck, pulmonary), epistaxis, erythema multiforme, erythema nodosum, exfoliative dermatitis, fever, fixed eruptions, flushing, gastrointestinal bleeding, gout (flare up), grand mal convulsion, gynecomastia, hallucinations, hearing loss, hematuria, hemolytic anemia, hemoptysis, hemorrhagic cystitis, hepatic failure (including fatal cases), hepatic necrosis, hepatitis, hiccup, hyperesthesia, hyperpigmentation, hypertension, hypertonia, hypoesthesia, hypotension, ileus, insomnia, interstitial nephritis, intestinal perforation, jaundice, joint stiffness, lethargy, lightheadedness, lipase increase, lymphadenopathy, malaise, manic reaction, marrow depression, migraine, moniliasis (oral, gastrointestinal, vaginal), mouth dryness, myalgia, myasthenia, myasthenia gravis (possible exacerbation), myocardial infarction, myoclonus, nephritis, nightmares, nystagmus, oral ulceration, pain (arm, back, breast, chest, epigastric, eye, extremities, foot, jaw, neck, oral mucosa), palpitation, pancreatitis, pancytopenia, paranoia, paresthesia, peripheral neuropathy, perspiration (increased), petechia, phlebitis, phobia, photosensitivity/phototoxicity reaction (see PRECAUTIONS) pleural effusion, polyuria, postural hypotension, prothrombin time prolongation, pseudomembranous colitis (the onset of symptoms may occur during or after antimicrobial treatment), pulmonary embolism, purpura, renal calculi, renal failure, respiratory arrest, respiratory distress, restlessness, serum sickness-like reaction, Stevens-Johnson syndrome, sweating, syncope, tachycardia, taste loss, tendonitis, tendon rupture, tinnitus, torsade de pointes, toxic epidermal necrolysis, toxic psychosis, tremor, twitching, unresponsiveness, urethral bleeding, urinary retention, urination (frequent), vaginal pruritus, vasculitis, ventricular ectopy, vesicles, visual acuity (decreased), visual disturbances (flashing lights, change in color perception, overbrightness of lights), weakness.

Reported Laboratory Changes with Proquin XR and Other Formulations of Ciprofloxacin

The following laboratory adverse events were reported for Proquin XR-treated patients during clinical trials: anemia, blood bilirubin increased, alanine aminotransferase increased, aspartate aminotransferase increased, platelet count decreased, and hematuria. All events were reported for <1% of Proquin XR-treated patients, except for hematuria (1.2%).

The following adverse laboratory changes, in alphabetical order, regardless of incidence or relationship to drug, have been reported in patients given ciprofloxacin (includes all formulations, all dosages, all drug-therapy durations, and all indications):

Decreases in blood glucose, BUN, hematocrit, hemoglobin, leukocyte counts, platelet counts, prothrombin time, serum albumin, serum potassium, total serum protein, uric acid.

Increases in alkaline phosphatase, ALT (SGPT), AST (SGOT), atypical lymphocyte counts, blood glucose, blood monocytes, BUN, cholesterol, eosinophils counts, LDH, platelet counts, prothrombin time, sedimentation rate, serum amylase, serum bilirubin, serum calcium, serum cholesterol, serum creatinine phosphokinase, serum creatinine, serum gamma-glutamyl transpeptidase (GGT), serum potassium, serum theophylline (in patients receiving theophylline concomitantly), serum triglycerides, uric acid.

Others: albuminuria, change in serum phenytoin, crystalluria, cylindruria, immature WBCs, leukocytosis, methemaglobinemia, pancytopenia.

OVERDOSAGE

In the event of an acute overdosage, the stomach should be emptied by inducing vomiting or by gastric lavage. The patient should be carefully observed and given supportive treatment. Adequate hydration must be maintained. Only a small amount of ciprofloxacin (<10%) is removed from the body after hemodialysis or peritoneal dialysis.

Serious adverse effects were not observed in rats receiving single oral doses of ciprofloxacin as high as 2,000 mg/kg.

DOSAGE AND ADMINISTRATION

Proquin XR and other oral formulations of ciprofloxacin are not interchangeable. Proquin XR should be administered orally once daily for 3 days with a main meal of the day, preferably the evening meal. Proquin XR should be administered at least 4 hours before or 2 hours after antacids containing magnesium or aluminum, sucralfate, VIDEX® (didanosine) chewable/buffered tablets or pediatric powder, metal cations such as iron, and multivitamin preparations containing zinc.

Proquin XR tablets should be taken whole and never split, crushed, or chewed. (See CLINICAL PHARMACOLOGY: Drug Interactions)

Impaired Renal Function:

Ciprofloxacin is eliminated primarily by renal excretion; however, the drug is also metabolized and partially cleared through the biliary system of the liver and through the intestine. These alternate pathways of drug elimination appear to compensate for the reduced renal excretion in patients with renal impairment. No dosage adjustment is required for patient with uUTI and mild to moderate renal impairment. The efficacy of Proquin XR has not been studied in patients with severe renal impairment. (See CLINICAL PHARMACOLOGY: Special Populations and PRECAUTIONS: Geriatric Use)

Impaired Liver Function:

No dosage adjustment is required with Proquin XR in patients with stable chronic cirrhosis. However, the pharmacokinetics of ciprofloxacin in patients with acute hepatic insufficiency have not been fully elucidated. (See CLINICAL PHARMACOLOGY: Special Populations)

HOW SUPPLIED

Proquin XR is available as blue film-coated tablets containing 500 mg ciprofloxacin. The tablet is debossed with "500"on one side and "DMI" on the other side.

Package | Strength | NDC Code
Bottles of 30 | 500 mg | 13913-001-30
Blister Packs of 3 | 500 mg | 13913-001-03

Store Proquin XR at 25°C (77°F); excursion permitted to 15-30°C (59-86°F) [see USP Controlled Room Temperature]

ANIMAL PHARMACOLOGY

There were no indications of gastrointestinal or other toxic effects due to oral administration of Proquin XR tablets to male and female beagle dogs at doses up to 1000 mg/day for 28 days (approximately 2.6- and 4.9-fold [male and female dogs, respectively] the recommended therapeutic dose based upon AUC measures of systemic exposure).

Ciprofloxacin and other quinolones have been shown to cause arthropathy in immature animals of most species tested. (See WARNINGS)

Crystalluria, sometimes associated with secondary nephropathy, occurs in laboratory animals dosed with the fluoroquinolone class of drugs. This is primarily related to the reduced solubility of ciprofloxacin under alkaline conditions, which predominate in the urine of test animals. In contrast, crystalluria is rare in man since human urine is typically acidic.

In mice, concomitant administration of nonsteroidal anti-inflammatory drugs such as phenylbutazone and indomethacin with quinolones has been reported to enhance the CNS stimulatory effects of quinolones.

Ocular toxicity seen with some related drugs has not been observed in ciprofloxacin-treated animals. There was no indication of ocular toxicity in the dog study cited above.

CLINICAL STUDIES

Proquin XR was evaluated for the treatment of uncomplicated urinary tract infections (acute cystitis) in a randomized, double-blind, controlled trial conducted in the US. This study compared Proquin XR (500 mg once daily for 3 days) with ciprofloxacin immediate-release tablets (CIPRO® 250 mg twice daily for 3 days). Of the 1,037 patients enrolled, 524 were randomly assigned to the Proquin XR treatment group and 513 were randomly assigned to the control group. A total of 272 (52%) patients in the Proquin XR group and 251 (49%) in the CIPRO group were evaluable for efficacy and included in the Per-Protocol population. The primary efficacy variable was bacteriologic eradication of the baseline organism(s) with no new infection at the Test-of-Cure (TOC) visit (Day 4 to 11 post-therapy).

The bacteriological eradication and clinical success rates were similar for both treatment groups. The eradication and clinical success rates and their corresponding 95% confidence intervals for the differences between rates (Proquin XR minus control group) are given in the following table:

Bacteriological Eradication and Clinical Cure Rates at the Test-of-Cure (TOC) Visit
 | Proquin XR 500 mg qd x 3 Days | CIPRO 250 mg bid x 3 Days
Randomized Patients | 524 | 513
Per Protocol Patients | 272 (52%) | 251 (49%)
Bacteriologic Eradication with no new infection at TOC | 212 / 272 (78%) | 193 / 251 (77%)
Bacteriologic Eradication with no new infection at TOC | (-6.2%, 8.2%)
Clinical Response at TOC | 233 / 272 (86%) | 216 / 251 (86%)
Clinical Response at TOC | (-6.4%, 5.6%)
Bacteriologic Eradication by organism* E. coli K. pneumonia | 211 / 222 (95%) 11 / 12 (92%) | 184 / 202 (91%) 10 / 13 (77%)
* Number of patients with specified baseline organism eradicated / Number of per-protocol patients with specified baseline organism.

The bacteriological eradication rates for baseline organisms at the TOC visit were 93% (254/272) for Proquin XR and 90% (225/251) for CIPRO. Of the patients with their baseline organism eradicated, new infections were detected in 42/254 (16.5%) Proquin XR-treated patients and 32/225 (14.2%) CIPRO-treated patients at the TOC visit. Gram-negative rods were responsible for new infections in 10 Proquin XR-treated patients and 7 CIPRO-treated patients, and Enterococcus species were isolated in 24 Proquin XR-treated patients, and 20 CIPRO-treated patients.

REFERENCES

1. National Committee for Clinical Laboratory Standards. Methods for Dilution Antimicrobial Susceptibility Tests for Bacteria That Grow Aerobically Sixth Edition. Approved Standard NCCLS Document M7-A6, Vol. 23, No. 2, NCCLS, Wayne, PA, January, 2003.
2. National Committee for Clinical Laboratory Standards. Performance Standards for Antimicrobial Disk Susceptibility Tests Eighth Edition. Approved Standard NCCLS Document M2-A8, Vol. 23, No. 1, NCCLS, Wayne, PA, January, 2003.

PROQUIN® XR (pro-kwin) (ciprofloxacin hydrochloride extended-release) Tablets

Read the Medication Guide that comes with Proquin® XR before you start taking it and each time you get a refill. There may be new information. This Medication Guide does not take the place of talking to your healthcare provider about your medical condition or your treatment.

What is the most important information I should know about Proquin® XR?

Proquin® XR belongs to a class of antibiotics called fluoroquinolones. Proquin® XR can cause side effects that may be serious or even cause death. If you get any of the following serious side effects, get medical help right away, and talk with your healthcare provider about whether you should continue to take Proquin® XR.

Tendon rupture or swelling of the tendon (tendonitis)

- Tendons are the tough cords of tissue that connects muscles to bones.
- Pain, swelling, inflammation of tendons including the back of the ankle (Achilles), shoulder, hand, or other tendon sites can happen in people of all ages who take fluoroquinolone antibiotics, including Proquin® XR. The risk of getting tendon problems is higher if you:
  - are over 60 years of age
  - are taking steroids (corticosteroids)
  - have had a kidney, heart or lung transplant
- Swelling of the tendon (tendonitis) and tendon rupture (breakage) have also happened in patients who take fluoroquinolones who do not have the above risk factors.
- Other reasons for tendon ruptures include:
  - physical activity or exercise
  - kidney failure
  - tendon problems in the past, such as in people with rheumatoid arthritis (RA).
- Call your healthcare provider right away at the first sign of tendon pain, swelling, or inflammation. Stop taking Proquin® XR until tendinitis or tendon rupture has been ruled out by your healthcare provider. Avoid exercise and using the affected area. The most common area of pain and swelling is the Achilles tendon at the back of your ankle. This can also happen with other tendons. Talk to your healthcare provider about the risk of tendon rupture with continued use of Proquin® XR. You may need a different antibiotic that is not a fluoroquinolone to treat your infection.
- Tendon rupture can happen while you are taking or after you have finished taking Proquin® XR. Tendon ruptures have happened up to several months after patients have finished taking their fluoroquinolone.
- Get medical help right away if you get any of the following signs or symptoms of a tendon rupture:
  - hear or feel a snap or pop in a tendon area
  - bruising right after an incident in a tendon area
  - unable to move the affected area or bear weight
- See the section "What are the possible side effects of Proquin® XR?" for more information about side effects.

What is Proquin® XR?

Proquin® XR is a fluoroquinolone antibiotic medicine used to treat simple bladder infections caused by certain germs called bacteria. It is not known if Proquin® XR is safe and works in treating any infections other than simple bladder infections. It is also not known if Proquin® XR is safe and works in children under 18 years of age. Children have a higher chance of getting bone, joint, or (musculoskeletal) problems while taking fluoroquinolone antibiotic medicines.

Sometimes infections are caused by viruses rather than by bacteria. Examples include viral infections in the sinuses and lungs, such as the common cold of flu. Antibiotics including Proquin® XR do not kill viruses.

Call your healthcare provider if you think your condition is not getting better while you are taking Proquin® XR.

Who should not take Proquin® XR?

Do not take Proquin® XR if you have ever had a severe allergic reaction to an antibiotic known as a fluoroquinolone, or are allergic to any of the ingredients in Proquin® XR. Ask your healthcare provider if you are not sure. See the list of ingredients in Proquin® XR at the end of this Medication Guide.

What should I tell my healthcare provider before taking Proquin® XR?

See "What is the most important information I should know about Proquin® XR?"

Tell your healthcare provider about all your medical conditions, including if you:

- have tendon problems
- have central nervous system problems (such as epilepsy)
- have nerve problems or anyone in your family has an irregular heartbeat, especially a condition called "QT prolongation."
- have a history of seizures
- have kidney problems
- have low blood potassium (hypokalemia)
- have rheumatoid arthritis (RA) or other history of joint problems
- have trouble swallowing pills
- are pregnant or planning to become pregnant. It is not known if Proquin® XR will harm your unborn child.
- are breast-feeding or planning to breast-feed. It is not known if Proquin® XR passes into breast milk. You and your healthcare provider should decide whether you will take Proquin® XR or breast-feed.

Tell your healthcare provider about all the medicines you take, including prescription and non-prescription medicines, vitamins, and herbal and dietary supplements. Proquin® XR and certain other medicines can affect each other. Especially tell your healthcare provider if you take:

- an NSAID (Non-Steroidal Anti-Inflammatory Drug). Many common medicines for pain relief are NSAIDs. Taking an NSAID while you take Proquin® XR or other fluoroquinolones may increase your risk of central nervous system effects and seizures. See "What are the possible side effects of Proquin® XR?"
- a blood thinner (warfarin, Coumadin, Jantoven)
- theophylline (Theo-24®, Elixophyllin®, Theochron®, Uniphyl®, Theolair®)
- glyburide (Micronase®, Glynase®, Diabeta®, Glucovance®)
- phenytoin (Fosphenytoin Sodium®, Cerebyx®, Dilantin-125®, Dilantin, Extended Phenytoin Sodium®, Prompt Phenytoin Sodium®, Phenytek®)
- products that contain caffeine
- a medicine to control your heart rate or rhythm (antiarrhythmics). See "What are the possible side effects of Proquin® XR?"
- an anti-psychotic medicine
- a tricyclic antidepressant
- a water pill (diuretic)
- a steroid medicine. Corticosteroids taken by mouth or by injection may increase the chance of tendon injury. See "What is the most important information I should know about Proquin® XR?"
- methotrexate (Trexall®)
- probenecid (Col-probenecid®)
- omeperazole (Nexium®, Nexium IV®, Zegrid®, Prilosec®)
- metoclopromide (Reglan®, Reglan ODT®)
- cyclosporine (Gengraf®, Sandimmune®, Neoral®)
- Certain medicines may keep Proquin® XR from working correctly. Take Proquin® XR at least 4 hours before or 2 hours after taking these products.
  - an antacid, multivitamin, or other product that contains magnesium, calcium, iron or zinc
  - sucralfate (Carafate)
  - didanosine (Videx®, Videx® EC)

Ask your healthcare provider if you are not sure if any of your medicines are listed above.

Know the medicines you take. Keep a list of your medicines and show it to your healthcare provider and pharmacist when you get a new medicine.

What if I receive a sample of Proquin® XR from my healthcare provider?

This sample contains only one dose for the first day of treatment of Proquin® XR and is not a complete treatment. To treat your bladder infection, you must take all 3 daily doses of Proquin® XR. You must fill a prescription from your healthcare provider for the remaining two daily doses before your next scheduled dose. Take all of your doses as prescribed by your healthcare provider, even if you are feeling better after the first dose. If you stop taking Proquin® XR before all of your doses are complete, Proquin® XR may not cure your bladder infection. It is not known if Proquin® XR will treat infections other than bladder infections. See also "How should I take Proquin® XR?"

How should I take Proquin® XR?

- Take Proquin® XR exactly as prescribed by your healthcare provider.
- Proquin® XR should be taken by mouth one time each day for 3 days
- Take Proquin® XR with your main meal of the day, preferably the evening meal. Try to take Proquin® XR at about the same time each day.
- Swallow Proquin® XR whole. Do not split, crush, or chew Proquin® XR. Tell your healthcare provider if you cannot swallow the tablets whole. Your healthcare provider will prescribe a different medicine for you.
- Drink plenty of fluids while taking Proquin® XR.
- Do not take Proquin® XR at the same time that you drink milk or juices with added calcium, unless you drink them with a main meal.
- Proquin® XR does not work as well if you take it without a meal.
- Do not skip any doses, or stop taking Proquin® XR even if you begin to feel better, until you finish your prescribed treatment, unless:
  - you have tendon effects (see "What is the most important information I should know about Proquin® XR?")
  - you have a serious allergic reaction (see "What are the possible side effects of Proquin® XR?"), or
  - your healthcare provider tells you to stop.
- This will help make sure that all of the bacteria are killed and lower the chance that the bacteria will become resistant to Proquin® XR. If this happens, Proquin® XR and other antibiotic medicines may not work in the future.
- Tell your healthcare provider if you do not feel better or if you get fever and back pain, while you are taking Proquin® XR or after you finish taking it. This may mean that your infection has not been cured and you may need another antibiotic medicine to treat your infection.
- If you miss a dose of Proquin® XR, take it as soon as your remember. Do not take more than one Proquin® XR tablet a day, even if you miss a dose.
- If you take too much, call your healthcare provider or get medical help immediately.

What should I avoid while taking Proquin® XR?

- Proquin® XR can make you feel dizzy and lightheaded. Do not drive, operate machinery, or do other activities that require mental alertness or coordination until you know how Proquin® XR affects you.
- Avoid sunlamps, tanning beds, and try to limit your time in the sun. Proquin® XR can make your skin sensitive to the sun (photosensitivity) and the light from the sunlamps and tanning beds. You could get severe sunburn, blisters or swelling of your skin. If you get any of these symptoms while taking Proquin® XR, call your healthcare provider right away. You should use a sunscreen, and wear a hat and clothes that cover your skin if you have to be in sunlight.

What are the possible side effects of Proquin® XR?

Proquin® XR can cause side effects that may be serious or even cause death. See "What is the most important information I should know about Proquin® XR?"

Other serious side effects of Proquin® XR include:

- Central Nervous System Effects: Tell your healthcare provider if you have a history of seizures. Ask your healthcare provider whether taking Proquin® XR will change your risk of having a seizure. Seizures have been reported in patients taking fluoroquinolone antibiotics including Proquin® XR.
  Central Nervous System (CNS) side effects may occur as soon as after taking the first dose of Proquin® XR. Talk to your healthcare provider right away if you experience any of these side effects, or other changes in mood or behavior:
  - feel dizzy
  - seizures
  - dizziness
  - hear voices, see things, or sense things that are not there (hallucinations)
  - feel restless
  - tremors
  - feel anxious or nervous
  - confusion
  - depression
  - trouble sleeping
  - nightmares
  - lightheadedness
  - feel more suspicious (paranoia)
  - suicidal thoughts or acts
- Serious allergic reactions: Allergic reactions can happen in people taking fluoroquinolones, including Proquin® XR, even after only one dose. Stop taking Proquin® XR and get emergency medical help right away if you get any of the following symptoms of a severe allergic reaction:
  - hives
  - trouble breathing or swallowing
  - swelling of the lips, tongue, face
  - throat tightness, hoarseness
  - rapid heartbeat
  - faint
  - yellowing of the skin or eyes. Stop taking Proquin® XR and tell your healthcare provider right away if you get yellowing of your skin or white part of your eyes, or if you have dark urine. These can be signs of a serious reaction to Proquin® XR (a liver problem).
- Skin rash: Skin rash may happen in people taking Proquin® XR, even after only one dose. Stop taking Proquin® XR at the first sign of a skin rash and call your healthcare provider. Skin rash may be sign of a more serious reaction to Proquin® XR.
- Serious heart rhythm changes (QT prolongation and torsades de pointes): Tell your healthcare provider right away if you have a change in your heart beat (get a fast or irregular heartbeat), or if you faint. Proquin® XR may cause a rare heart problem known as prolongation of the QT interval. This condition can cause an abnormal heartbeat and can be very dangerous. The chances of this happening are higher in people:
  - who are elderly
  - with a family history of prolonged QT interval,
  - with low potassium (hypokalemia),
  - who take certain medicines to control heart rhythm (antiarrhythmics).
- Intestine infection (Pseudomembranous colitis): Pseudomembranous colitis can happen with most antibiotics, including Proquin® XR. Call your healthcare provider right away if you get watery diarrhea, diarrhea that does not go away, or bloody stools. You may have stomach cramps and a fever. Pseudomembranous colitis can happen 2 or more months after you have finished your antibiotic.
- Changes in sensation and possible nerve damage (Peripheral Neuropathy): Damage to the nerves in arms, hands, legs, or feet can happen in people taking fluoroquinolones, including Proquin® XR. Talk with your healthcare provider right away if you get any of the following symptoms of peripheral neuropathy in your arms, hands, legs, or feet:
  - pain
  - burning
  - tingling
  - numbness
  - weakness
  Proquin® XR may need to be stopped to prevent nerve damage.
- Low blood sugar (hypoglycemia): People taking fluoroquinolone medicines such as Proquin® XR with oral anti-diabetes medicines glyburide (Micronase®, Glynase®, Diabeta®, Glucovance®) can get low blood sugar (hypoglycemia). Follow your healthcare provider's instructions for how often to check your blood sugar. Tell your healthcare provider if you get low blood sugar with Proquin® XR. Your antibiotic medicine may need to be changed.
- Sensitivity to sunlight (photosensitivity): See "What should I avoid while taking Proquin® XR?"

The most common side effects of Proquin® XR include:

- yeast infection
- inflamed nose and throat
- headache
- feeling an urgent need to urinate

These are not all the possible side effects of Proquin® XR. Tell your healthcare provider about any side effect that bothers you or that does not go away.

Call your doctor for medical advice about side effects. You may report side effects to FDA at 1-800-FDA-1088.

How should I store Proquin® XR?

- Store Proquin® XR at 59-86°F (15-30°C).
- Keep Proquin® XR and all medicines out of the reach of children.

General Information about Proquin® XR

Medicines are sometimes prescribed for purposes other than those listed in a Medication Guide. Do not use Proquin® XR for a condition for which it is not prescribed. Do not share Proquin® XR with other people, even if they have the same symptoms that you have. It may harm them.

This Medication Guide summarizes the most important information about Proquin® XR. If you would like more information about Proquin® XR, talk with your healthcare provider. You can ask your healthcare provider or pharmacist for information about Proquin® XR that is written for healthcare professionals. For more information go to www.proquinxr.com or call 1-866-458-6389.

What are the ingredients in Proquin® XR?

- Active Ingredient: ciprofloxacin hydrochloride
- Inactive Ingredient: film coating, magnesium stearate, polyethylene oxide, and povidone.

Revised November 2008
PRO-001-C.1

Proquin® XR is a registered trademark of Depomed, Inc.
©2005-2008 Depomed, Inc
Rx Only

Proquin® XR
Depomed, Inc.
1360 O'Brien Drive
Menlo Park, CA 94025-1436
1-866-458-6389

This Medication Guide has been approved by the U.S. Food and Drug Administration.

PRINCIPAL DISPLAY PANEL

NDC 13913-001-30 - Bottles of 30 (500 mg Tablets)